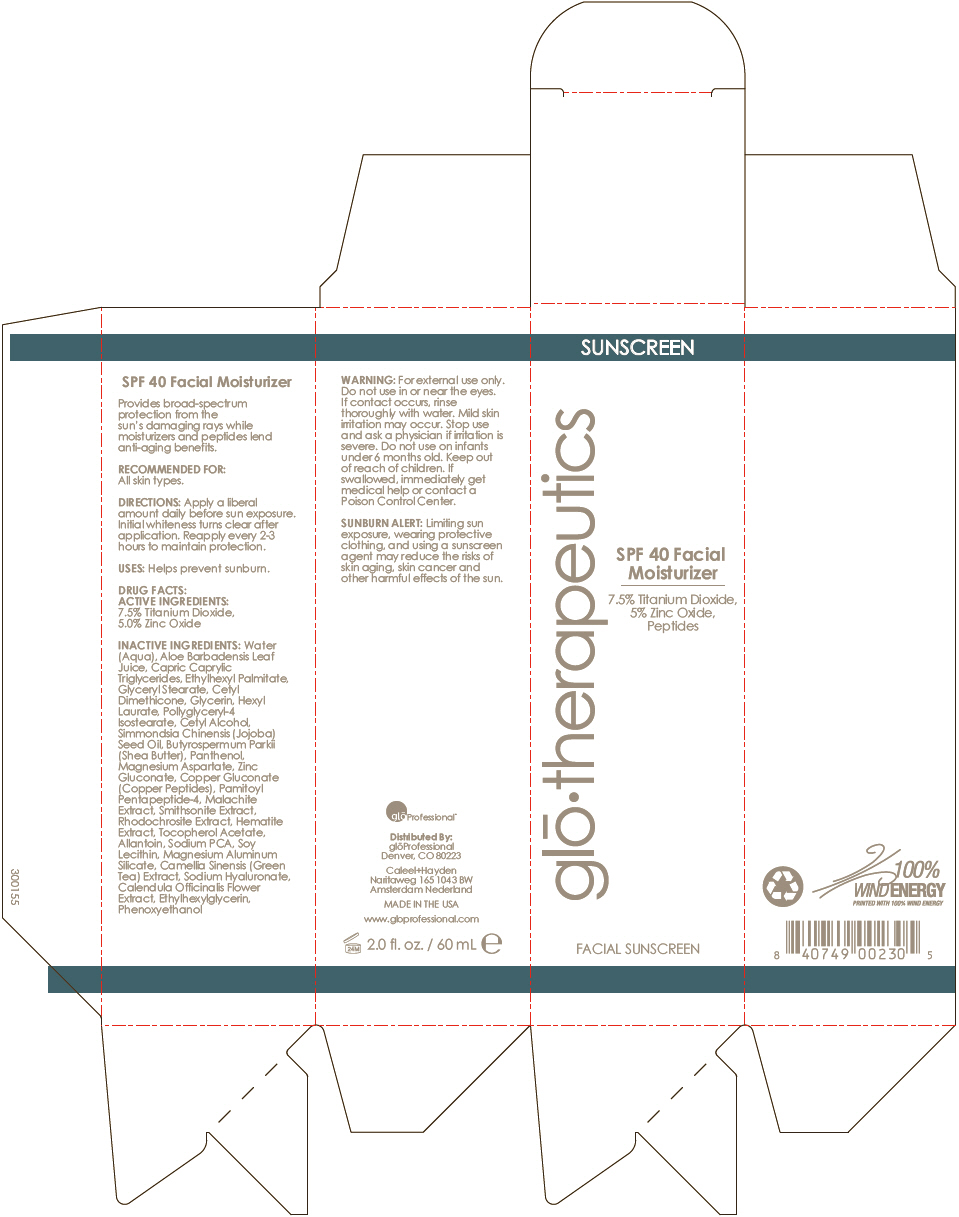 DRUG LABEL: SPF-40 facial moisturizer
NDC: 55789-0101 | Form: LOTION
Manufacturer: Mineral Fusion brands
Category: otc | Type: HUMAN OTC DRUG LABEL
Date: 20130405

ACTIVE INGREDIENTS: Zinc Oxide 5 g/100 mL; Titanium dioxide 7.5 g/100 mL
INACTIVE INGREDIENTS: ethylhexyl palmitate; glyceryl monostearate; cetyl dimethicone 25; glycerin; hexyl laurate; aloe vera leaf; polyglyceryl-4 isostearate; medium-chain triglycerides; cetyl alcohol; shea butter; panthenol; magnesium aspartate; zinc gluconate; jojoba oil; tocopherol; copper gluconate; hyaluronate sodium; palmitoyl pentapeptide-4; ethylhexylglycerin; allantoin; sodium pyrrolidone carboxylate; lecithin, soybean; magnesium aluminum silicate; green tea leaf; phenoxyethanol

SPF-40 facial moisturizer

DRUG FACTS

PURPOSE

Provides broad-spectrum protection from the sun's damaging rays while moisturizers and peptides lend anti-aging benefits.

RECOMMENDED FOR

All skin types.

DIRECTIONS

Apply a liberal amount daily before sun exposure. Initial whiteness turns clear after application. Reapply every 2-3 hours to maintain protection.

USES

Helps prevent sunburn.

ACTIVE INGREDIENTS

7.5% Titanium Dioxide, 5.0% Zinc Oxide

INACTIVE INGREDIENTS

Water (Aqua), Aloe Barbadensis Leaf Juice, Capric Caprylic Triglycerides, Ethylhexyl Palmitate, Glyceryl Stearate, Cetyl Dimethicone, Glycerin, Hexyl Laurate, Pollyglyceryl-4 Isostearate, Cetyl Alcohol, Simmondsia Chinensis (Jojoba) Seed Oil, Butyrospermum Parkii (Shea Butter), Panthenol, Magnesium Aspartate, Zinc Gluconate, Copper Gluconate (Copper Peptides), Pamitoyl Pentapeptide-4, Malachite Extract, Smithsonite Extract, Rhodochrosite Extract, Hematite Extract, Tocopherol Acetate, Allantoin, Sodium PCA, Soy Lecithin, Magnesium Aluminum Silicate, Camellia Sinensis (Green Tea) Extract, Sodium Hyaluronate, Calendula Officinalis Flower Extract, Ethylhexylglycerin, Phenoxyethanol

WARNING

For external use only.

Do not use in or near the eyes. If contact occurs, rinse thoroughly with water.

STOP USE

Mild skin irritation may occur. Stop use and ask a physician if irritation is severe.

Do not use on infants under 6 months old.

Keep out of reach of children. If swallowed, immediately get medical help or contact a Poison Control Center.

SUNBURN ALERT

Limiting sun exposure, wearing protective clothing, and using a sunscreen agent may reduce the risks of skin aging, skin cancer and other harmful effects of the sun.

Distributed By:
glōProfessional
Denver, CO 80223

PRINCIPAL DISPLAY PANEL - 60 mL Tube Carton

SUNSCREEN

glō•therapeutics

SPF 40 Facial
Moisturizer

7.5% Titanium Dioxide,
5% Zinc Oxide,
Peptides

FACIAL SUNSCREEN